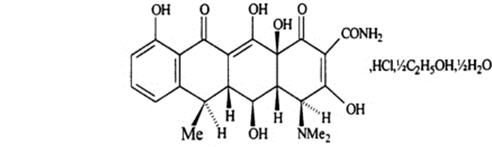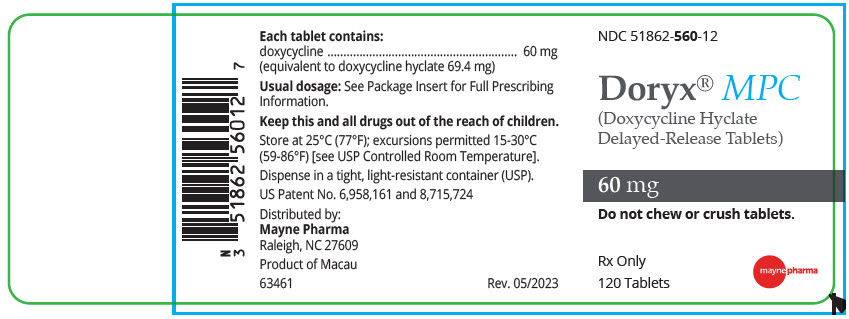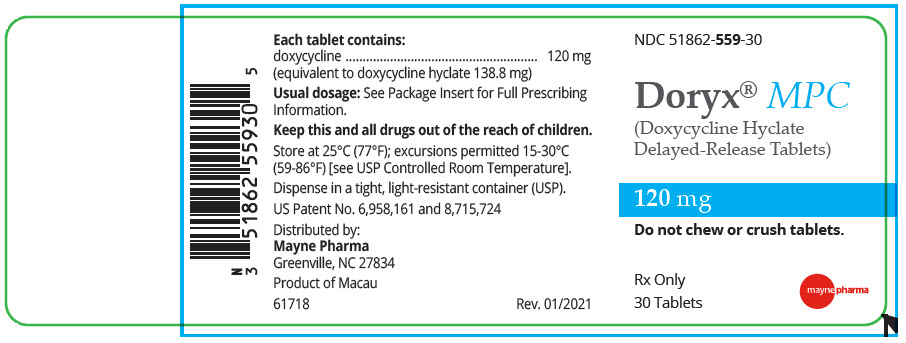 DRUG LABEL: DORYX MPC
NDC: 51862-560 | Form: TABLET, DELAYED RELEASE
Manufacturer: Mayne Pharma Commercial LLC
Category: prescription | Type: HUMAN PRESCRIPTION DRUG LABEL
Date: 20260216

ACTIVE INGREDIENTS: DOXYCYCLINE HYCLATE 60 mg/1 1
INACTIVE INGREDIENTS: LACTOSE MONOHYDRATE; MICROCRYSTALLINE CELLULOSE; SODIUM LAURYL SULFATE; SODIUM CHLORIDE; TALC; ANHYDROUS LACTOSE; STARCH, CORN; CROSPOVIDONE (120 .MU.M); MAGNESIUM STEARATE

HIGHLIGHTS OF PRESCRIBING INFORMATION

These highlights do not include all the information needed to use DORYX MPC safely and effectively. See full prescribing information for DORYX MPC
DORYX MPC (doxycycline hyclate delayed-release tablets), for oral use.
Initial U.S. Approval: 1967

RECENT MAJOR CHANGES

Warnings and Precautions, Severe Skin Reactions (5.5) | 03/2025

1 INDICATIONS AND USAGE

DORYX MPC is a tetracycline class drug indicated for:

- Rickettsial Infections (1.1)
- Sexually Transmitted Infections (1.2)
- Respiratory Tract Infections(1.3)
- Specific Bacterial Infections (1.4)
- Ophthalmic Infections (1.5)
- Anthrax, Including Inhalational Anthrax (Post-Exposure) (1.6)
- Alternative Treatment for Selected Infections when Penicillin is Contraindicated (1.7)
- Adjunctive Therapy in Acute Intestinal Amebiasis and Severe Acne (1.8)
- Prophylaxis of Malaria (1.9)

Usage

To reduce the development of drug-resistant bacteria and maintain the effectiveness of doxycycline hyclate and other antibacterial drugs, DORYX MPC Tablets should be used only to treat or prevent infections that are proven or strongly suspected to be caused by bacteria. (1.10)

2 DOSAGE AND ADMINISTRATION

- Important Dosage and Administration Instructions:
  - DORYX MPC is not substitutable on a mg per mg basis with other oral doxycyclines. (2.1)
  - Do not chew or crush tablets. (2.1)
- Dosage in Adult Patients
  - The usual dosage of DORYX MPC is 240 mg on the first day of treatment (administered 120 mg every 12 hours) followed by a maintenance dose of 120 mg daily. (2.3)
  - In the management of more severe infections (particularly chronic infections of the urinary tract), 120 mg every 12 hours is recommended. (2.3)
- Dosage in Pediatric Patients
  - For all pediatric patients weighing less than 45 kg with severe or life threatening infections (e.g., anthrax, Rocky Mountain spotted fever), the recommended dosage of DORYX MPC is 2.6 mg per kg of body weight administered every 12 hours. Pediatric patients weighing 45 kg or more should receive the adult dose. (2.4)
  - For pediatric patients with less severe disease (greater than 8 years of age and weighing less than 45 kg), the recommended dosage schedule of DORYX MPC is 5.3 mg per kg of body weight divided into two doses on the first day of treatment, followed by a maintenance dose of 2.6 mg per kg of body weight (given as a single daily dose or divided into twice daily doses). For pediatric patients weighing over 45 kg, the usual adult dose should be used. (2.4)

- See Full Prescribing Information for additional indication specific dosage information and important administration instructions for DORYX MPC. (2.2, 2.5, 2.6)

3 DOSAGE FORMS AND STRENGTHS

DORYX MPC Delayed-Release Tablets 60 mg (3)

4 CONTRAINDICATIONS

Doxycycline is contraindicated in persons who have shown hypersensitivity to any of the tetracyclines. (4)

5 WARNINGS AND PRECAUTIONS

- The use of drugs of the tetracycline-class during tooth development (last half of pregnancy, infancy and childhood to the age of 8 years) may cause permanent discoloration of the teeth (yellow-gray-brown). (5.1)
- Clostridioides difficile-Associated Diarrhea. Evaluate patients if diarrhea occurs. (5.2)
- Photosensitivity manifested by an exaggerated sunburn reaction has been observed in some individuals taking tetracyclines. Limit sun exposure. (5.3)
- Overgrowth of non-susceptible organisms, including fungi, may occur. If such infections occur, discontinue use and institute appropriate therapy. (5.4)

6 ADVERSE REACTIONS

Adverse reactions observed in patients receiving tetracyclines include anorexia, nausea, vomiting, diarrhea, rash, photosensitivity, urticaria, and hemolytic anemia. (6)

To report SUSPECTED ADVERSE REACTIONS, contact Mayne Pharma at 1-844-825-8500 or FDA at 1-800-FDA-1088 or www.fda.gov/medwatch.

7 DRUG INTERACTIONS

- Patients who are on anticoagulant therapy may require downward adjustment of their anticoagulant dosage (7.1)
- Avoid co-administration of tetracyclines with penicillin (7.2)
- Absorption of tetracyclines, including DORYX MPC is impaired by antacids containing aluminum, calcium, or magnesium, bismuth subsalicylate and iron-containing preparations (7.3)
- Concurrent use of tetracyclines, including DORYX MPC may render oral contraceptives less effective (7.4)
- Barbiturates, carbamazepine, and phenytoin decrease the half-life of doxycycline (7.5)

8 USE IN SPECIFIC POPULATIONS

- Tetracycline-class drugs can cause fetal harm when administered to a pregnant woman, but data for doxycycline are limited. (5.6, 8.1)
- Tetracyclines are excreted in human milk; however, the extent of absorption of doxycycline in the breastfed infant is not known. DORYX MPC use during nursing should be avoided if possible. (8.2)

FULL PRESCRIBING INFORMATION

1 INDICATIONS AND USAGE

1.1 Rickettsial Infections

DORYX MPC is indicated for treatment of Rocky Mountain spotted fever, typhus fever and the typhus group, Q fever, rickettsialpox, and tick fevers caused by Rickettsiae.

1.2 Sexually Transmitted Infections

DORYX MPC is indicated for treatment of the following sexually transmitted infections:

- Uncomplicated urethral, endocervical or rectal infections in adults caused by Chlamydia trachomatis.
- Nongonococcal urethritis caused by Ureaplasma urealyticum.
- Lymphogranuloma venereum caused by Chlamydia trachomatis.
- Granuloma inguinale caused by Klebsiella granulomatis.
- Uncomplicated gonorrhea caused by Neisseria gonorrhoeae.
- Chancroid caused by Haemophilus ducreyi.

1.3 Respiratory Tract Infections

DORYX MPC is indicated for treatment of the following respiratory tract infections:

- Respiratory tract infections caused by Mycoplasma pneumoniae.
- Psittacosis (ornithosis) caused by Chlamydophila psittaci.
- Because many strains of the following groups of microorganisms have been shown to be resistant to doxycycline, culture and susceptibility testing are recommended.
- Doxycycline is indicated for treatment of infections caused by the following microorganisms, when bacteriological testing indicates appropriate susceptibility to the drug:
  - Respiratory tract infections caused by Haemophilus influenzae.
  - Respiratory tract infections caused by Klebsiellaspecies.
  - Upper respiratory infections caused by Streptococcus pneumoniae.

1.4 Specific Bacterial Infections

DORYX MPC is indicated for treatment of the following specific bacterial infections:

- Relapsing fever due to Borrelia recurrentis.
- Plague due to Yersinia pestis.
- Tularemia due to Francisella tularensis.
- Cholera caused by Vibrio cholerae.
- Campylobacter fetus infections caused by Campylobacter fetus.
- Brucellosis due to Brucellaspecies (in conjunction with streptomycin).
- Bartonellosis due to Bartonella bacilliformis.

Because many strains of the following groups of microorganisms have been shown to be resistant to doxycycline, culture and susceptibility testing are recommended.

DORYX MPC is indicated for treatment of infections caused by the following gram-negative microorganisms, when bacteriological testing indicates appropriate susceptibility to the drug:

- Escherichia coli
- Enterobacter aerogenes
- Shigella species
- Acinetobacter species
- Urinary tract infections caused by Klebsiella species.

1.5 Ophthalmic Infections

DORYX MPC is indicated for treatment of the following ophthalmic infections:

- Trachoma caused by Chlamydia trachomatis, although the infectious agent is not always eliminated as judged by immunofluorescence.
- Inclusion conjunctivitis caused by Chlamydia trachomatis.

1.6 Anthrax Including Inhalational Anthrax (Post-Exposure)

DORYX MPC is indicated for treatment of Anthrax due to Bacillus anthracis, including inhalational anthrax (post-exposure): to reduce the incidence or progression of disease following exposure to aerosolized Bacillus anthracis.

1.7 Alternative Treatment for Selected Infections when Penicillin is Contraindicated

DORYX MPC is indicated as an alternative treatment for the following selected infections when penicillin is contraindicated:

- Syphilis caused by Treponema pallidum.
- Yaws caused by Treponema pallidumsubspecies pertenue.
- Listeriosis due to Listeria monocytogenes.
- Vincent's infection caused by Fusobacterium fusiforme.
- Actinomycosis caused by Actinomyces israelii.
- Infections caused by Clostridiumspecies.

1.8 Adjunctive Therapy for Acute Intestinal Amebiasis and Severe Acne

In acute intestinal amebiasis, DORYX MPC may be a useful adjunct to amebicides.

In severe acne, DORYX MPC may be useful adjunctive therapy.

1.9 Prophylaxis of Malaria

DORYX MPC is indicated for the prophylaxis of malaria due to Plasmodium falciparumin short-term travelers (less than 4 months) to areas with chloroquine and/or pyrimethamine-sulfadoxine resistant strains [ see Dosage and Administration (2.2)and Patient Counseling Information (17)].

1.10 Usage

To reduce the development of drug-resistant bacteria and maintain the effectiveness of DORYX MPC and other antibacterial drugs, DORYX MPC should be used only to treat or prevent infections that are proven or strongly suspected to be caused by susceptible bacteria. When culture and susceptibility information are available, they should be considered in selecting or modifying antibacterial therapy. In the absence of such data, local epidemiology and susceptibility patterns may contribute to the empiric selection of therapy.

2 DOSAGE AND ADMINISTRATION

2.1 Important Dosage and Administration Instructions

- DORYX MPC is not substitutable on a mg per mg basis with other oral doxycyclines. To avoid prescribing errors, do not substitute DORYX MPC for other oral doxycyclines on a mg per mg basis because of differing bioavailability.
- Do not chew or crush tablets.
- The recommended dosage, frequency of administration and weight-based dosage recommendations of DORYX MPC differ from that of the other tetracyclines [ see Dosage and Administration (2.2, 2.3, 2.4)] .Exceeding the recommended dosage may result in an increased incidence of adverse reactions.
- Administer DORYX MPC with an adequate amount of fluid to wash down the drug and reduce the risk of esophageal irritation and ulceration [ see Adverse Reactions (6)].
- If gastric irritation occurs, DORYX MPC may be given with food or milk [see Clinical Pharmacology (12.3)] .

2.2 Switching from DORYX to DORYX MPC

When switching from DORYX to DORYX MPC :

- A 60 mg dose of DORYX MPC will replace a 50 mg dose of DORYX
- A 120 mg dose of DORYX MPC will replace a 100 mg dose of DORYX

2.3 Dosage in Adult Patients

- The usual dosage of DORYX MPC is 240 mg on the first day of treatment (administered 120 mg every 12 hours) followed by a maintenance dose of 120 mg daily. The maintenance dose may be administered as a single dose or as 60 mg every 12 hours.
- In the management of more severe infections (particularly chronic infections of the urinary tract), 120 mg every 12 hours is recommended.
- For certain selected specific indications, the recommended duration or dosage and duration of DORYX MPC in adult patients are as follows:
  1. Streptococcal infections, therapy should be continued for 10 days.
  2. Uncomplicated urethral, endocervical, or rectal infection caused by C. trachomatis: 120 mg, by mouth, twice-a-day for 7 days.
  3. Uncomplicated gonococcal infections in adults (except anorectal infections in men): 120 mg, by mouth, twice-a-day for 7 days. As an alternate single visit dose, administer 360 mg followed in one hour by a second 360 mg dose.
  4. Nongonococcal urethritis (NGU) caused by C. trachomatisand U. urealyticum: 120 mg, by mouth, twice-a-day for 7 days.
  5. Syphilis – early: Patients who are allergic to penicillin should be treated with doxycycline 120 mg, by mouth, twice-a-day for 2 weeks.
  6. Syphilis of more than one year's duration: Patients who are allergic to penicillin should be treated with doxycycline 120 mg, by mouth, twice-a-day for 4 weeks.
  7. Acute epididymo-orchitis caused by N. gonorrhoeae: 120 mg, by mouth, twice-a-day for at least 10 days.
  8. Acute epididymo-orchitis caused by C. trachomatis: 120 mg, by mouth, twice-a-day for at least 10 days

2.4 Dosage in Pediatric Patients

- For all pediatric patients weighing less than 45 kg with severe or life threatening infections (e.g., anthrax, Rocky Mountain spotted fever), the recommended dosage of DORYX MPC is 2.6 mg per kg of body weight administered every 12 hours. Pediatric patients weighing 45 kg or more should receive the adult dose [see Warnings and Precautions (5.1)] .
- For pediatric patients with less severe disease (greater than 8 years of age and weighing less than 45 kg), the recommended dosage schedule of DORYX MPC is 5.3 mg per kg of body weight divided into two doses on the first day of treatment, followed by a maintenance dose of 2.6 mg per kg of body weight (given as a single daily dose or divided into twice daily doses). For pediatric patients weighing over 45 kg, the usual adult dose should be used.

2.5 Dosage for Prophylaxis of Malaria

For adults, the recommended dose of DORYX MPC is 120 mg daily.

For pediatric patients 8 years of age and older, the recommended dosage of DORYX MPC is 2.4 mg per kg of body weight administered once daily. Pediatric patients weighing 45 kg or more should receive the adult dose .

Prophylaxis should begin 1 or 2 days before travel to the malarious area. Prophylaxis should be continued daily during travel in the malarious area and for 4 weeks after the traveler leaves the malarious area.

2.6 Dosage for Inhalational Anthrax (Post-Exposure)

For adults, the recommended dosage is 120 mg, of DORYX MPC, by mouth, twice-a-day for 60 days.

For pediatric patients weighing less than 45 kg, the recommended dosage of DORYX MPC is 2.6 mg per kg of body weight, by mouth, twice-a-day for 60 days. Pediatric patients weighing 45 kg or more should receive the adult dose.

3 DOSAGE FORMS AND STRENGTHS

DORYX MPC (doxycycline hyclate delayed-release tablets), 60 mg are white, oval tablets containing yellow pellets and debossed with "D6" on one face and plain on the other. Each tablet contains doxycycline 60 mg (equivalent to doxycycline hyclate 69.4 mg).

4 CONTRAINDICATIONS

DORYX MPC is contraindicated in persons who have shown hypersensitivity to any of the tetracyclines.

5 WARNINGS AND PRECAUTIONS

5.1 Tooth Development

The use of drugs of the tetracycline-class during tooth development (last half of pregnancy, infancy and childhood to the age of 8 years) may cause permanent discoloration of the teeth (yellow-gray-brown). This adverse reaction is more common during long-term use of the drugs but it has been observed following repeated short-term courses. Enamel hypoplasia has also been reported. Use DORYX MPC in pediatric patients 8 years of age or less only when the potential benefits are expected to outweigh the risks in severe or life-threatening conditions (e.g., anthrax, Rocky Mountain spotted fever), particularly when there are no alternative therapies.

5.2 Clostridioidesdifficile Associated Diarrhea

Clostridioides difficileassociated diarrhea (CDAD) has been reported with use of nearly all antibacterial agents, including DORYX MPC Tablets, and may range in severity from mild diarrhea to fatal colitis. Treatment with antibacterial agents alters the normal flora of the colon leading to overgrowth of C. difficile.

C. difficileproduces toxins A and B which contribute to the development of CDAD. Hypertoxin producing strains of C. difficilecause increased morbidity and mortality, as these infections can be refractory to antimicrobial therapy and may require colectomy. CDAD must be considered in all patients who present with diarrhea following antibacterial use. Careful medical history is necessary since CDAD has been reported to occur over two months after the administration of antibacterial agents.

If CDAD is suspected or confirmed, ongoing antibacterial use not directed against C. difficilemay need to be discontinued. Appropriate fluid and electrolyte management, protein supplementation, antibacterial treatment of C .difficile , and surgical evaluation should be instituted as clinically indicated.

5.3 Photosensitivity

Photosensitivity manifested by an exaggerated sunburn reaction has been observed in some individuals taking tetracyclines. Patients apt to be exposed to direct sunlight or ultraviolet light should be advised that this reaction can occur with tetracycline drugs, and treatment should be discontinued at the first evidence of skin erythema.

5.4 Potential for Microbial Overgrowth

DORYX MPC may result in overgrowth of non-susceptible organisms, including fungi. If such infections occur, discontinue use and institute appropriate therapy.

5.5 Severe Skin Reactions

Severe skin reactions, such as exfoliative dermatitis, erythema multiforme, Stevens-Johnson syndrome, toxic epidermal necrolysis, and drug reaction with eosinophilia and systemic symptoms (DRESS) have been reported in patients receiving doxycycline. Fixed drug eruptions have occurred with doxycycline and have been associated with worsening severity upon subsequent administrations, including generalized bullous fixed drug eruption [See Adverse Reactions (6)]. If severe skin reactions occur, discontinue DORYX MPC immediately and institute appropriate therapy.

5.6 Intracranial Hypertension

Intracranial hypertension (IH, pseudotumor cerebri) has been associated with the use of tetracycline including DORYX MPC. Clinical manifestations of IH include headache, blurred vision, diplopia, and vision loss; papilledema can be found on fundoscopy. Women of childbearing age who are overweight or have a history of IH are at greater risk for developing tetracycline associated IH. Avoid concomitant use of isotretinoin and DORYX MPC because isotretinoin is also known to cause pseudotumor cerebri.

Although IH typically resolves after discontinuation of treatment, the possibility for permanent visual loss exists. If visual disturbance occurs during treatment, prompt ophthalmologic evaluation is warranted. Since intracranial pressure can remain elevated for weeks after drug cessation patients should be monitored until they stabilize.

5.7 Skeletal Development

All tetracyclines form a stable calcium complex in any bone-forming tissue. A decrease in fibula growth rate has been observed in prematures given oral tetracycline in doses of 25 mg/kg every six hours. This reaction was shown to be reversible when the drug was discontinued. [ See Use in Specific Populations (8.1)].

5.8 Antianabolic Action

The antianabolic action of the tetracyclines may cause an increase in BUN. Studies to date indicate that this does not occur with the use of doxycycline in patients with impaired renal function.

5.9 Malaria

Doxycycline offers substantial but not complete suppression of the asexual blood stages of Plasmodiumstrains.

Doxycycline does not suppress P. falciparum'ssexual blood stage gametocytes. Subjects completing this prophylactic regimen may still transmit the infection to mosquitoes outside endemic areas.

5.10 Development of Drug-Resistant Bacteria

Prescribing DORYX MPC in the absence of a proven or strongly suspected bacterial infection or a prophylactic indication is unlikely to provide benefit to the patient and increases the risk of the development of drug-resistant bacteria.

5.11 Laboratory Monitoring for Long-Term Therapy

In long-term therapy, periodic laboratory evaluation of organ systems, including hematopoietic, renal, and hepatic studies should be performed.

6 ADVERSE REACTIONS

The following adverse reactions have been identified during post-approval use of doxycycline. Because these reactions are reported voluntarily from a population of uncertain size, it is not always possible to reliably estimate their frequency or establish a causal relationship to drug exposure.

Due to oral doxycycline's virtually complete absorption, side effects to the lower bowel, particularly diarrhea, have been infrequent. The following adverse reactions have been observed in patients receiving tetracyclines:

Gastrointestinal:Anorexia, nausea, vomiting, diarrhea, glossitis, dysphagia, enterocolitis, inflammatory lesions (with monilial overgrowth) in the anogenital region, and pancreatitis. Hepatotoxicity has been reported. These reactions have been caused by both the oral and parenteral administration of tetracyclines. Esophagitis and esophageal ulcerations have been reported in patients receiving capsule and tablet forms of drugs in the tetracycline-class. Most of these patients took medications immediately before going to bed [ see Dosage and Administration (2.1)].

Skin:Maculopapular and erythematous rashes, Stevens-Johnson syndrome, toxic epidermal necrolysis, exfoliative dermatitis, erythema multiforme, and fixed drug eruption have been reported. Photosensitivity is discussed above [ see Warnings and Precautions (5.3)].

Renal:Rise in BUN has been reported and is apparently dose-related [ see Warnings and Precautions (5.8)].

Hypersensitivity reactions:Urticaria, angioneurotic edema, anaphylaxis, anaphylactoid purpura, serum sickness, pericarditis, and exacerbation of systemic lupus erythematosus.

Blood:Hemolytic anemia, thrombocytopenia, neutropenia, and eosinophilia have been reported.

Intracranial Hypertension:Intracranial hypertension (IH, pseudotumor cerebri) has been associated with the use of tetracycline [ See Warnings and Precautions (5.6)]

Thyroid Gland Changes:When given over prolonged periods, tetracyclines have been reported to produce brown-black microscopic discoloration of thyroid glands. No abnormalities of thyroid function are known to occur.

Psychiatric:Depression, anxiety, suicidal ideation, insomnia, abnormal dreams, hallucination

7 DRUG INTERACTIONS

7.1 Anticoagulant Drugs

Because tetracyclines have been shown to depress plasma prothrombin activity, patients who are on anticoagulant therapy may require downward adjustment of their anticoagulant dosage.

7.2 Penicillin

Since bacteriostatic drugs may interfere with the bactericidal action of penicillin, it is advisable to avoid giving tetracyclines, including DORYX MPC in conjunction with penicillin.

7.3 Antacids and Iron Preparations

Absorption of tetracyclines including DORYX MPC is impaired by antacids containing aluminum, calcium, or magnesium, bismuth subsalicylate, and iron-containing preparations.

7.4 Oral Contraceptives

Concurrent use of tetracyclines, including DORYX MPC may render oral contraceptives less effective.

7.5 Barbiturates and anti-epileptics

Barbiturates, carbamazepine, and phenytoin decrease the half-life of doxycycline.

7.6 Drug/Laboratory Test Interactions

False elevations of urinary catecholamines may occur due to interference with the fluorescence test.

8 USE IN SPECIFIC POPULATIONS

8.1 Pregnancy

Risk Summary

There are no adequate studies on the use of doxycycline in pregnant women. The vast majority of reported experience with doxycycline during human pregnancy is short-term, first trimester exposure. There are no human data available to assess the effects of long-term therapy of doxycycline in pregnant women such as that proposed for the treatment of anthrax exposure. An expert review of published data on experiences with doxycycline use during pregnancy by TERIS - the Teratogen Information System - concluded that therapeutic doses during pregnancy are unlikely to pose a substantial teratogenic risk (the quantity and quality of data were assessed as limited to fair), but the data are insufficient to state that there is no risk.^1In the U.S. general population the estimated background risk of major birth defects and miscarriage in clinically recognized pregnancies is 2-4% and 15-20%, respectively [ see Data].

Clinical Considerations

Embryo/Fetal Risk

Results of animal studies indicate that tetracyclines cross the placenta, are found in fetal tissues, and can have toxic effects on the developing fetus (often related to retardation of skeletal development). Evidence of embryotoxicity also has been noted in animals treated early in pregnancy. If any tetracycline is used during pregnancy or if the patient becomes pregnant while taking these drugs, the patient should be apprised of the potential hazard to the fetus. [ see Warnings and Precautions (5.1, 5.6)].

Data

Human Data

A case-control study (18,515 mothers of infants with congenital anomalies and 32,804 mothers of infants with no congenital anomalies) shows a weak but marginally statistically significant association with total malformations and use of doxycycline anytime during pregnancy. Sixty-three (0.19%) of the controls and 56 (0.30%) of the cases were treated with doxycycline. This association was not seen when the analysis was confined to maternal treatment during the period of organogenesis (i.e., in the second and third months of gestation), with the exception of a marginal relationship with neural tube defect based on only two-exposed cases.^2

A small prospective study of 81 pregnancies describes 43 pregnant women treated for 10 days with doxycycline during early first trimester. All mothers reported their exposed infants were normal at 1 year of age.^3

8.2 Lactation

Risk Summary

Tetracyclines are excreted in human milk, however, the extent of absorption of tetracyclines including doxycycline, by the breastfed infant is not known. Short-term use by lactating women is not contraindicated. The effects of prolonged exposure to doxycycline on breast milk production and breast fed neonates, infants and children are unknown.^4The developmental and health benefits of breast feeding should be considered along with the mother's clinical need for DORYX MPC and any potential adverse effects on the breast fed child from DORYX MPC or from the underlying maternal condition [ see Warnings and Precautions (5.1, 5.6)].

8.4 Pediatric Use

Because of the effects of drugs of the tetracycline-class on tooth development and growth, use DORYX MPC in pediatric patients 8 years of age or less only when the potential benefits are expected to outweigh the risks in severe or life-threatening conditions (e.g., anthrax, Rocky Mountain spotted fever), particularly when there are no alternative therapies [ see Warnings and Precautions (5.1, 5.6)and Dosage and Administration (2.1, 2.4)].

8.5 Geriatric Use

Clinical studies of DORYX MPC did not include sufficient numbers of subjects aged 65 and over to determine whether they respond differently from younger subjects. Other reported clinical experience has not identified differences in responses between the elderly and younger patients. DORYX MPC Tablets each contain less than 10 mg of sodium.

10 OVERDOSAGE

In case of overdosage, discontinue medication, treat symptomatically and institute supportive measures. Dialysis does not alter serum half-life and thus would not be of benefit in treating cases of overdosage.

11 DESCRIPTION

Doryx MPC (doxycycline hyclate delayed-release tablets) for oral use, contain doxycycline hyclate, a tetracycline class drug synthetically derived from oxytetracycline, in a delayed-release formulation consisting of pellets with a modified polymer enteric coat that has increased acid resistance.

The structural formula for doxycycline hyclate is:

with a molecular formula of C22H24N2O8, HCl, ½ C2H6O, ½ H2O and a molecular weight of 512.9. The chemical name for doxycycline hyclate is [4S(4aR,5S,5aR,6R,12aS)]-4-(dimethylamino)-1,4,4a,5,5a,6,11,12a-octahydro-3,5,10,12,12a-pentahydroxy-6-methyl-1,11-deoxonaphthacene-2-carboxamide monohydrochloride, compound with ethyl alcohol (2:1), monohydrate. Doxycycline hyclate is a yellow crystalline powder soluble in water and in solutions of alkali hydroxides and carbonates. Doxycycline has a high degree of lipid solubility and a low affinity for calcium binding. It is highly stable in normal human serum. Doxycycline will not degrade into an epianhydro form.

Each tablet contains doxycycline 60 mg (equivalent to doxycycline hyclate 69.4 mg) or doxycycline 120 mg (equivalent to doxycycline hyclate 138.8 mg). Inactive ingredients in the tablet formulation are: lactose monohydrate; microcrystalline cellulose; sodium lauryl sulfate; sodium chloride; talc; anhydrous lactose; corn starch; crospovidone; magnesium stearate; cellulosic polymer coating.

Each DORYX MPC 60 mg Tablet contains 3.6 mg (0.157 mEq) of sodium.

Each DORYX MPC 120 mg Tablet contains 7.2 mg (0.313 mEq) of sodium.

12 CLINICAL PHARMACOLOGY

12.1 Mechanism of Action

Doxycycline is a tetracycline-class antimicrobial drug [ see Microbiology (12.4)].

12.3 Pharmacokinetics

Effect of Food

Following administration of a single dose of DORYX MPC under fasting conditions, the AUCinfand Cmaxwere 26.7 mcg-h/mL and 1.6 mcg/mL, respectively. The Tmax was 2.8 hours. In a single-dose study to evaluate the relative bioavailability in healthy adult subjects under fasted conditions, DORYX MPC 120 mg Tablets were found to be bioequivalent to Doryx 100 mg Tablets. When a single dose of DORYX MPC 120 mg Tablet was administered with a standardized high-fat high-calorie meal, (937kcal consisting of approximately 55% fat, 30% carbohydrate and 15% protein), the Cmaxwas approximately 30% lower, but there was no significant difference in the AUCinfcompared to administration under fasting conditions [see Dosage and Administration (2.1)] .

Absorption

Doxycycline is virtually completely absorbed after oral administration.

Elimination

Tetracyclines are concentrated in bile by the liver and excreted in the urine and feces at high concentrations and in a biologically active form. Excretion of doxycycline by the kidney is about 40%/72 hours in individuals with a creatinine clearance of about 75 mL/min. This percentage may fall as low as 1-5%/72 hours in individuals with a creatinine clearance below 10 mL/min.

Specific Populations

Patients with Renal Impairment

Studies have shown no significant difference in the serum half-life of doxycycline (range 18 to 22 hours) in individuals with normal and severely impaired renal function. Hemodialysis does not alter the serum half-life.

Pediatric Patients

Population pharmacokinetic analysis of sparse concentration-time data of doxycycline. following standard of care intravenous and oral dosing in 44 children (2-18 years of age) showed that allometrically-scaled clearance of doxycycline in children ≥2 to ≤8 years of age (median [range] 3.58 [2.27-10.82] L/h/70 kg, N=11) did not differ significantly from children >8 to 18 years of age (3.27 [1.11-8.12] L/h/70 kg, N=33). For pediatric patients weighing ≤45 kg, body weight normalized doxycycline CL in those ≥2 to ≤8 years of age (median [range] 0.071 [0.041-0.202] L/kg/h, N=l0) did not differ significantly from those >8 to 18 years of age (0.081 [0.035-0.126] L/kg/h, N=8). In pediatric patients weighing >45 kg no clinically significant differences in body weight normalized doxycycline CL were observed between those ≥2 to ≤8 years (0.050 L/kg/h, N=l) and those >8 years of age (0.044 [0.014-0. 121] L/kg/h, N=25). No clinically significant difference in CL differences between oral and IV were observed in the small cohort of pediatric patients who received the oral (N=l9) or IV (N=21) formulation alone.

12.4 Microbiology

Mechanism of Action

Doxycycline inhibits bacterial protein synthesis by binding to the 30S ribosomal subunit. Doxycycline has bacteriostatic activity against a broad range of Gram-positive and Gram-negative bacteria.

Resistance

Cross-resistance between tetracyclines is common.

Antimicrobial Activity

Doxycycline has been shown to be active against most isolates of the following bacteria, both in vitroand in clinical infections [see Indications and Usage (1)].

Gram-negative Bacteria

Acinetobacterspecies
Bartonella bacilliformis
Brucella species
Campylobacter fetus
Enterobacter aerogenes
Escherichia coli
Francisella tularensis
Haemophilus ducreyi
Haemophilus influenzae
Klebsiella granulomatis
Klebsiella species
Neisseria gonorrhoeae
Shigella species
Vibrio cholerae
Yersinia pestis

Gram-positive Bacteria

Bacillus anthracis
Listeria monocytogenes
Streptococcus pneumoniae

Anaerobic Bacteria

Clostridiumspecies
Fusobacterium fusiforme
Propionibacterium acnes

Other Bacteria

Norcardiaeand other aerobic Actinomycesspecies
Borrelia recurrentis
Chlamydophila psittaci
Chlamydia trachomatis
Mycoplasma pneumonia
Rickettsiae
Treponema pallidum
Treponema pallidum subspecies pertenue
Ureaplasma urealyticum

Parasites

Balantidium coli
Entamoeba species
Plasmodium falciparum [Doxycycline has been found to be active against the asexual erythrocytic forms of Plasmodium falciparum but not against the gametocytes of P. falciparum. The precise mechanism of action of the drug is not known.]

Susceptibility Testing

For specific information regarding susceptibility test interpretive criteria and associated test methods and quality control standards recognized by FDA for this drug, please see: https://www.fda.gov/STIC.

13 NONCLINICAL TOXICOLOGY

13.1 Carcinogenesis, Mutagenesis, Impairment of Fertility

Long-term studies in animals to evaluate carcinogenic potential of doxycycline have not been conducted. However, there has been evidence of oncogenic activity in rats in studies with the related antibiotics, oxytetracycline (adrenal and pituitary tumors) and minocycline (thyroid tumors). Likewise, although mutagenicity studies of doxycycline have not been conducted, positive results in in vitromammalian cell assays have been reported for related antibacterials (tetracycline, oxytetracycline).

Doxycycline administered orally at dosage levels as high as 250 mg/kg/day had no apparent effect on the fertility of female rats. Effect on male fertility has not been studied.

13.2 Animal Toxicology and/or Pharmacology

Hyperpigmentation of the thyroid has been produced by members of the tetracycline-class in the following species: in rats by oxytetracycline, doxycycline, tetracycline PO4, and methacycline; in minipigs by doxycycline, minocycline, tetracycline PO4, and methacycline; in dogs by doxycycline and minocycline; in monkeys by minocycline.

Minocycline, tetracycline PO4, methacycline, doxycycline, tetracycline base, oxytetracycline HCl, and tetracycline HCl, were goitrogenic in rats fed a low iodine diet. This goitrogenic effect was accompanied by high radioactive iodine uptake. Administration of minocycline also produced a large goiter with high radioiodine uptake in rats fed a relatively high iodine diet.

Treatment of various animal species with this class of drugs has also resulted in the induction of thyroid hyperplasia in the following: in rats and dogs (minocycline); in chickens (chlortetracycline); and in rats and mice (oxytetracycline). Adrenal gland hyperplasia has been observed in goats and rats treated with oxytetracycline.

Results of animal studies indicate that tetracyclines cross the placenta and are found in fetal tissues.

15 REFERENCES

1. Friedman JM, Polifka JE. Teratogenic Effects of Drugs. A Resource for Clinicians (TERIS). Baltimore, MD: The Johns Hopkins University Press: 2000: 149-195. The TERIS (Teratogen Information System) is available at: http://www.micromedexsolutions.com/ (cited: 2016 Jan).
2. Cziezel AE and Rockenbauer M. Teratogenic study of doxycycline. Obstet Gynecol1997; 89: 524-528.
3. Horne HW Jr. and Kundsin RB. The role of mycoplasma among 81 consecutive pregnancies: a prospective study. Int J Fertil1980; 25: 315-317.
4. Drugs and Lactation Database (LactMed) [Internet]. Bethesda (MD): National Library of Medicine (US); [Last Revision Date 2015 March 10; cited 2016 Jan]. Doxycycline; LactMed Record Number: 100; [about 3 screens]. Available from: http://toxnet.nlm.nih.gov/newtoxnet/lactmed.htm

16 HOW SUPPLIED/STORAGE AND HANDLING

DORYX MPC (doxycycline hyclate delayed-release tablets), 60 mg are white, oval tablets containing yellow pellets and debossed with "D6" on one face and plain on the other. Each tablet contains doxycycline 60 mg (equivalent to doxycycline hyclate 69.4 mg).

The 60 mg tablet is supplied in bottles of 60 tablets (NDC 51862-560-60) and 120 tablets (NDC 51862-560-12).

STORAGE AND HANDLING

Store at 25° C (77° F); excursions permitted to 15°C to 30° C (59°F to 86° F) [see USP Controlled Room Temperature]. Dispense in a tight, light-resistant container (USP).

17 PATIENT COUNSELING INFORMATION

Advise patients taking DORYX MPC for malaria prophylaxis:

- that no present-day antimalarial agent, including doxycycline, guarantees protection against malaria.
- to avoid being bitten by mosquitoes by using personal protective measures that help avoid contact with mosquitoes, especially from dusk to dawn (for example, staying in well-screened areas, using mosquito nets, covering the body with clothing, and using an effective insect repellent).
- that doxycycline prophylaxis:
  - should begin 1 to 2 days before travel to the malarious area,
  - should be continued daily while in the malarious area and after leaving the malarious area,
  - should be continued for 4 further weeks to avoid development of malaria after returning from an endemic area,
  - should not exceed 4 months.

Advise all patients taking DORYX MPC:

- to avoid excessive sunlight or artificial ultraviolet light while receiving doxycycline and to discontinue therapy if phototoxicity (for example, skin eruptions, etc.) occurs. Sunscreen or sunblock should be considered [ see Warnings and Precautions (5.3)]
- to drink fluids liberally along with DORYX MPC to reduce the risk of esophageal irritation and ulceration [ see Adverse Reactions (6)]
- that the absorption of tetracyclines is reduced when taken with foods, especially those that contain calcium. [ see Drug Interactions (7.3)]
- that if gastric irritation occurs, DORYX MPC may be given with food or milk [ see Clinical Pharmacology (12.3)]
- that the absorption of tetracyclines is reduced when taken with antacids containing aluminum, calcium or magnesium, bismuth subsalicylate, and iron-containing preparations [ see Drug Interactions (7.3)].
- that the use of doxycycline might increase the incidence of vaginal candidiasis.

Advise patients that diarrhea is a common problem caused by antibacterial drugs which usually ends when the antibacterial is discontinued. Sometimes after starting treatment with antibacterial drugs, patients can develop watery and bloody stools (with or without stomach cramps and fever) even as late as two or more months after having taken the last dose of antibacterial. If this occurs, patients should contact their physician as soon as possible.

Patients should be counseled that antibacterial drugs including DORYX MPC should only be used to treat bacterial infections. They do not treat viral infections (e.g., the common cold). When DORYX MPC is prescribed to treat a bacterial infection, patients should be told that although it is common to feel better early in the course of therapy, the medication should be taken exactly as directed. Skipping doses or not completing the full course of therapy may (1) decrease the effectiveness of the immediate treatment and (2) increase the likelihood that bacteria will develop resistance and will not be treatable by DORYX MPC or other antibacterial drugs in the future.

Distributed by:
Mayne Pharma
Raleigh, NC 27609

61596

PRINCIPAL DISPLAY PANEL - 60 mg Tablet Bottle Label

NDC 51862-560-12

Doryx®MPC
(Doxycycline Hyclate
Delayed-Release Tablets)

60 mg

Do not chew or crush tablets.

Rx Only
120 Tablets

mayne pharma

PRINCIPAL DISPLAY PANEL - 120 mg Tablet Bottle Label

NDC 51862-559-30

Doryx®MPC
(Doxycycline Hyclate
Delayed-Release Tablets)

120 mg

Do not chew or crush tablets.

Rx Only
30 Tablets

mayne pharma